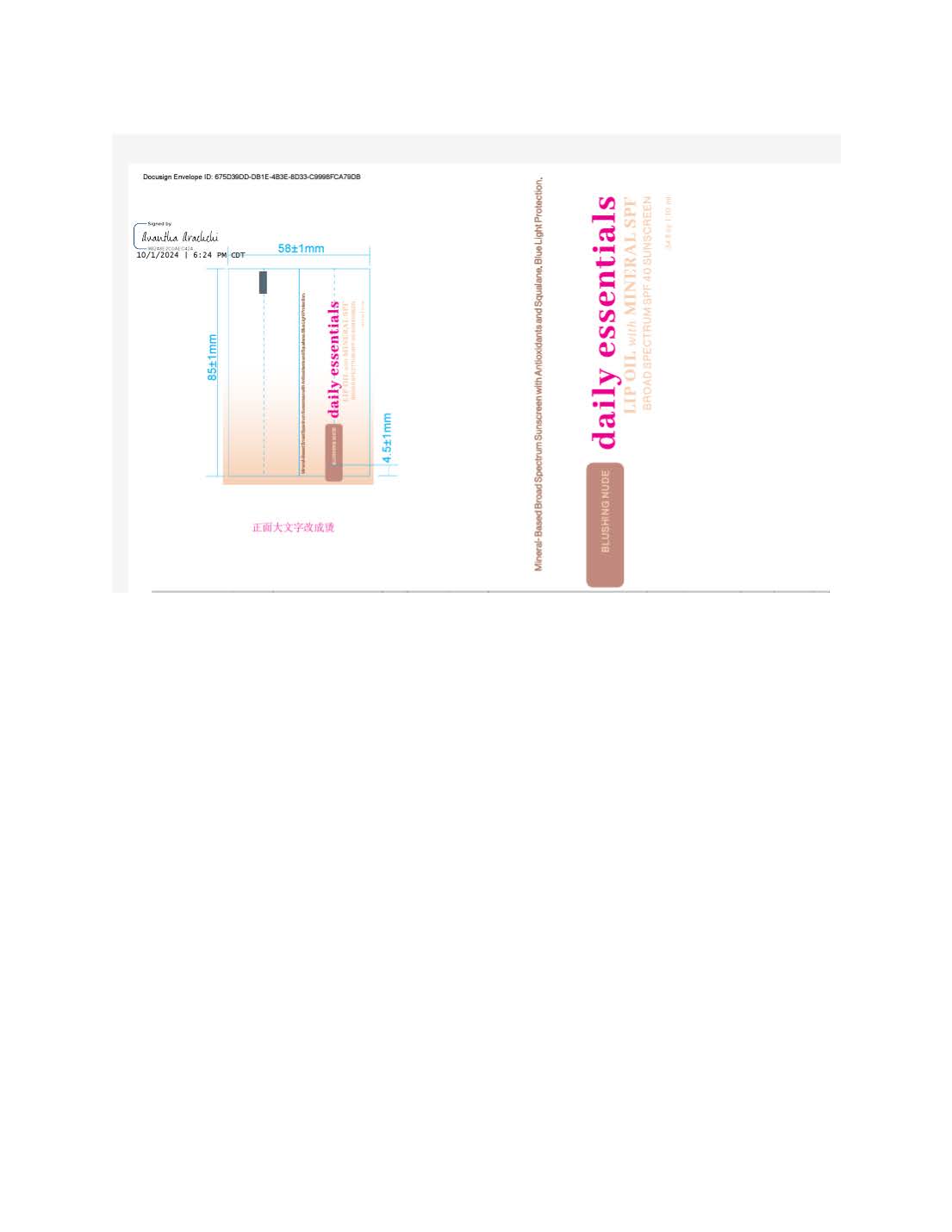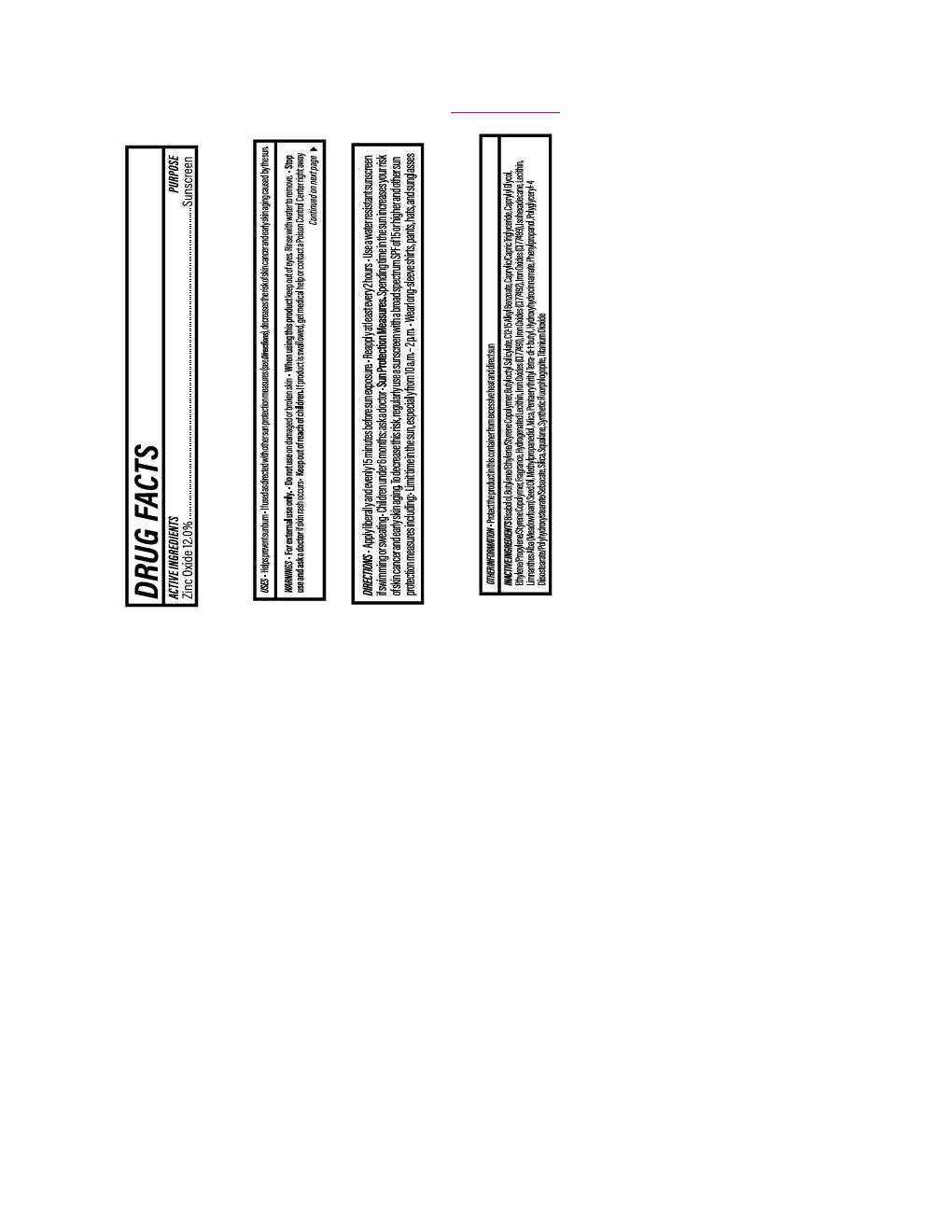 DRUG LABEL: Daily Essential Lip Oil Blushing Nude
NDC: 84891-2107 | Form: LOTION
Manufacturer: Solarium Brands LLC
Category: otc | Type: HUMAN OTC DRUG LABEL
Date: 20251117

ACTIVE INGREDIENTS: ZINC OXIDE 132 mg/1 mL
INACTIVE INGREDIENTS: MICA; FERRIC OXIDE YELLOW; SILICON DIOXIDE; FERROSOFERRIC OXIDE; METHYLPROPANEDIOL; LECITHIN, SOYBEAN; SQUALANE; BUTYLOCTYL SALICYLATE; PHENYLPROPANOL; TITANIUM DIOXIDE; PENTAERYTHRITYL TETRA-DI-T-BUTYL HYDROXYHYDROCINNAMATE; ISOHEXADECANE; FERRIC OXIDE RED; ALKYL (C12-15) BENZOATE; CAPRYLIC/CAPRIC TRIGLYCERIDE; CAPRYLYL GLYCOL; POLYGLYCERYL-4 DIISOSTEARATE/POLYHYDROXYSTEARATE/SEBACATE; LIMNANTHES ALBA (MEADOWFOAM) SEED OIL; .ALPHA.-BISABOLOL, (+)-

Daily Essential Lip Oil Blushing Nude